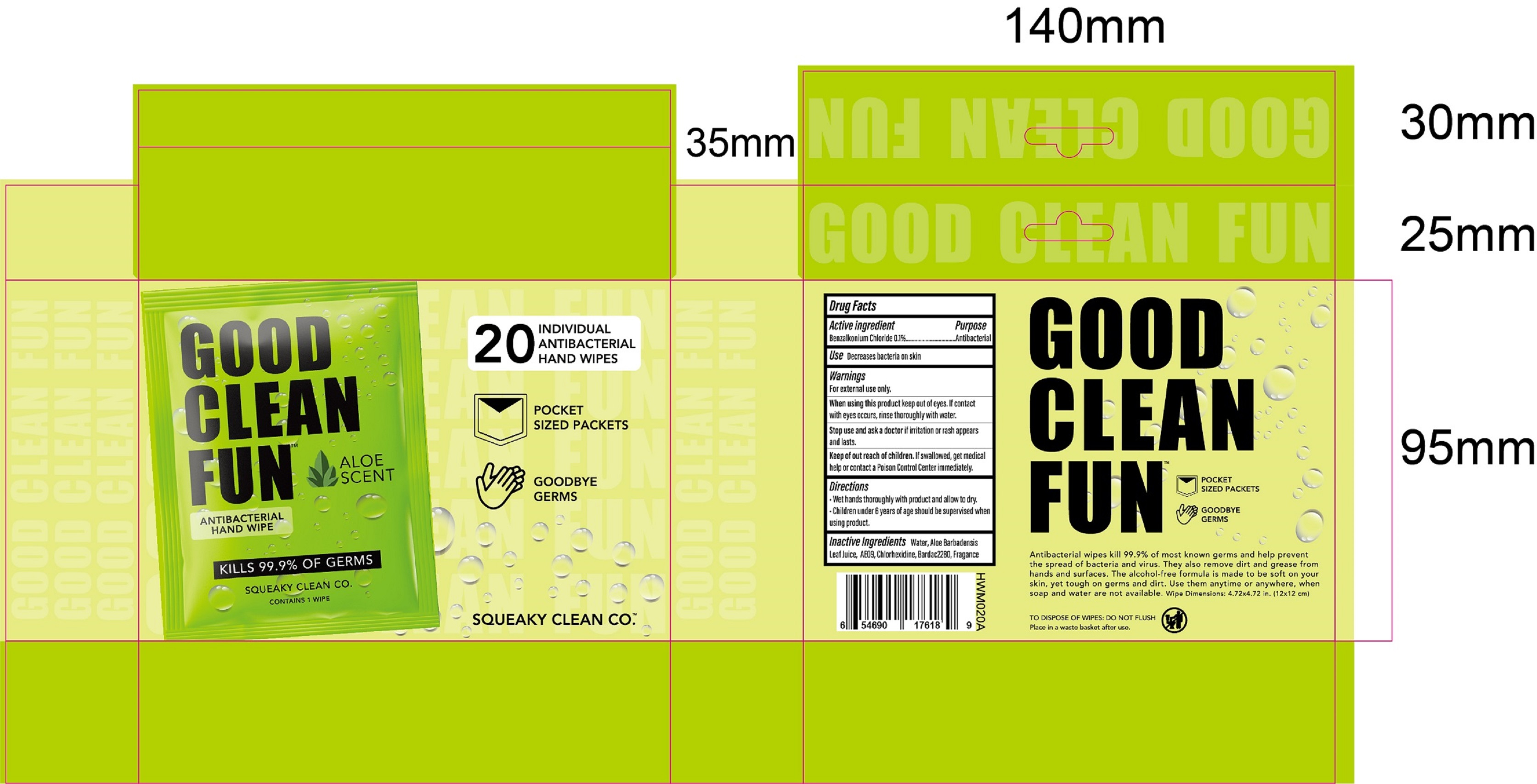 DRUG LABEL: 20 pack Individual Antibacterial Hand Wipes - Aloe
NDC: 77827-020 | Form: CLOTH
Manufacturer: Tianjin Lantian Bishui Technology Co,. Ltd.
Category: otc | Type: HUMAN OTC DRUG LABEL
Date: 20200823

ACTIVE INGREDIENTS: BENZALKONIUM CHLORIDE 0.1 g/100 1
INACTIVE INGREDIENTS: ALOE; ALOE VERA LEAF; FECLOBUZONE; CHLORHEXIDINE; WATER; DIDECYLDIMONIUM CHLORIDE

77827-020-20 20 pack Individual Antibacterial Hand Wipes - Aloe Tianjin Lantian Bishui Technology Co,. Ltd.

Active Ingredient(s)

Benzalkonium Chloride 0.1%. Purpose: Antibacterial

Purpose

Antibacterial, HAND WIPES

Use

Decreases bacteria on skin.

Warnings

For external use only.

Do not use

- Children under 6 years of age should be supervised when using product.

When using this product keep out of eyes, If contact with eyes occurs, rinse thoroughly with water.

Stop use and ask a doctor if irritation or rash appears and lasts.

Keep out of reach of children. If swallowed, get medical help or contact a Poison Control Center immediately.

Directions

- Wet hands thoroughly with product and allow to dry.
- Children under 6 years of age should be supervised when using product.

Other information

Children under 6 years of age should be supervised when using product.. Store in cool, dry place. High temperatures may reduce shelf life or dry out wipes. May discolor some fabrics and wood surface.

Inactive ingredients

Water, Aloe Barbadensis Leaf Juice, AE09, Chlorhexidine, Bardac 2280, Fragrance.

Package Label - Principal Display Panel

20 Hand Wipes NDC:77827-020-20